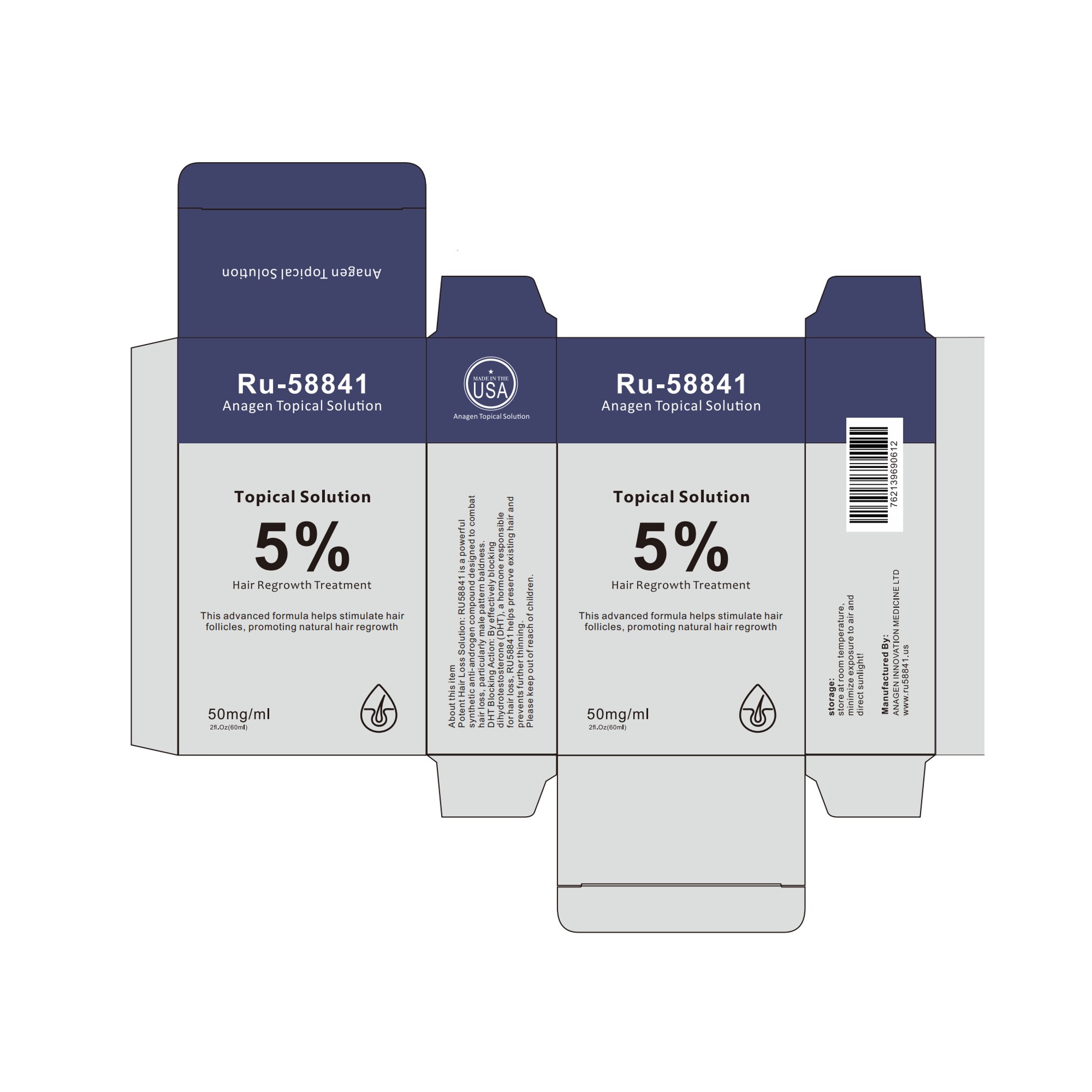 DRUG LABEL: Anagen Topical Solution
NDC: 85475-001 | Form: SOLUTION
Manufacturer: ANAGEN INNOVATION MEDICINE LTD
Category: otc | Type: HUMAN OTC DRUG LABEL
Date: 20250417

ACTIVE INGREDIENTS: RU-58841 5 g/100 mL
INACTIVE INGREDIENTS: LACTIC ACID; WATER; MENTHOL; GLYCERIN; ALCOHOL; CITRIC ACID

Anagen Topical Solution

ACTIVE INGREDIENT

ru-58841 5%

PURPOSE

Hair Regrowth Treatment

INDICATIONS AND USAGE

Hair Regrowth Treatment
For Research Purpose OnlyNot For Human Consumption

KEEP OUT OF REACH OF CHILDREN SECTION

WARNINGS

For external use only

DOSAGE AND ADMINISTRATION

Take an appropriate amount of solution and apply it to the root of the head

INACTIVE INGREDIENT

GLYCERIN
ALCOHOL
LEVOMENTHOL